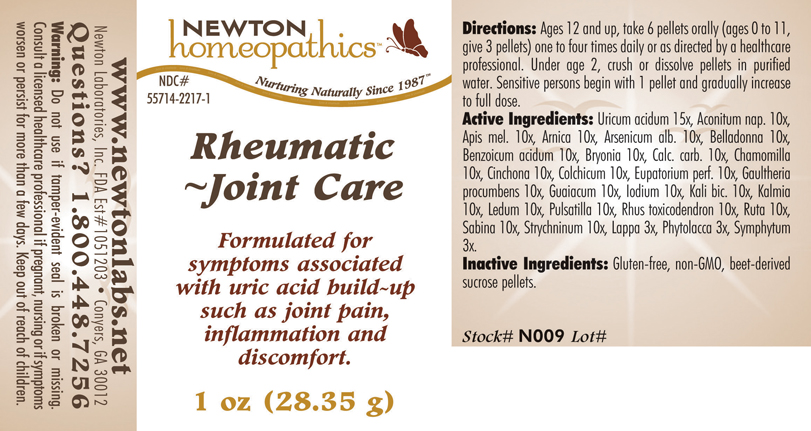 DRUG LABEL: Rheumatic - Joint Care 
NDC: 55714-2217 | Form: PELLET
Manufacturer: Newton Laboratories, Inc.
Category: homeopathic | Type: HUMAN OTC DRUG LABEL
Date: 20110301

ACTIVE INGREDIENTS: Uric Acid 15 [hp_X]/1 g; Aconitum Napellus 10 [hp_X]/1 g; Apis Mellifera 10 [hp_X]/1 g; Arnica Montana 10 [hp_X]/1 g; Arsenic Trioxide 10 [hp_X]/1 g; Atropa Belladonna 10 [hp_X]/1 g; Benzoic Acid 10 [hp_X]/1 g; Bryonia Alba Root 10 [hp_X]/1 g; Oyster Shell Calcium Carbonate, Crude 10 [hp_X]/1 g; Matricaria Recutita 10 [hp_X]/1 g; Cinchona Officinalis Bark 10 [hp_X]/1 g; Colchicum Autumnale Bulb 10 [hp_X]/1 g; Eupatorium Perfoliatum Flowering Top 10 [hp_X]/1 g; Gaultheria Procumbens Top 10 [hp_X]/1 g; Guaiacum Officinale Resin 10 [hp_X]/1 g; Iodine 10 [hp_X]/1 g; Potassium Dichromate 10 [hp_X]/1 g; Kalmia Latifolia Leaf 10 [hp_X]/1 g; Ledum Palustre Twig 10 [hp_X]/1 g; Pulsatilla Vulgaris 10 [hp_X]/1 g; Toxicodendron Pubescens Leaf 10 [hp_X]/1 g; Ruta Graveolens Flowering Top 10 [hp_X]/1 g; Juniperus Sabina Leafy Twig 10 [hp_X]/1 g; Strychnine 10 [hp_X]/1 g; Arctium Lappa Root 3 [hp_X]/1 g; Phytolacca Americana Root 3 [hp_X]/1 g; Comfrey Root 3 [hp_X]/1 g
INACTIVE INGREDIENTS: Sucrose

Rheumatic - Joint Care

INDICATIONS & USAGE SECTION

Rheumatic - Joint Care Formulated for symptoms associated with uric acid build-up such as joint pain, inflammation and discomfort.

DOSAGE & ADMINISTRATION SECTION

Directions: Ages 12 and up, take 6 pellets orally (ages 0 to 11, give 3 pellets) one to four times daily or as directed by a healthcare professional. Under age 2, crush or dissolve pellets in purified water. Sensitive persons begin with 1 pellet and gradually increase to full dose.

OTC - ACTIVE INGREDIENT SECTION

Uricum acidum 15x, Aconitum nap. 10x, Apis mel. 10x, Arnica 10x, Arsenicum alb. 10x, Belladonna 10x, Benzoicum acidum 10x, Bryonia 10x, Calc. carb. 10x, Chamomilla 10x, Cinchona 10x, Colchicum 10x, Eupatorium perf. 10x, Gaultheria procumbens 10x, Guaiacum 10x, Iodium 10x, Kali bic. 10x, Kalmia 10x, Ledum 10x, Pulsatilla 10x, Rhus toxicodendron 10x, Ruta 10x, Sabina 10x, Strychninum 10x, Lappa 3x, Phytolacca 3x, Symphytum 3x.

OTC - PURPOSE SECTION

Formulated for symptoms associated with uric acid build-up such as joint pain, inflammation and discomfort.

INACTIVE INGREDIENT SECTION

Inactive Ingredients: Gluten-free, non-GMO, beet-derived sucrose pellets.

QUESTIONS SECTION

www.newtonlabs.net Newton Laboratories, Inc. FDA Est # 1051203 - Conyers, GA 30012
Questions? 1.800.448.7256

WARNINGS SECTION

Warning: Do not use if tamper - evident seal is broken or missing. Consult a licensed healthcare professional if pregnant, nursing or if symptoms worsen or persist for more than a few days. Keep out of reach of children

OTC - PREGNANCY OR BREAST FEEDING SECTION

Consult a licensed healthcare professional if pregnant, nursing or if symptoms worsen or persist for more than a few days.

OTC - KEEP OUT OF REACH OF CHILDREN SECTION

Keep out of reach of children.